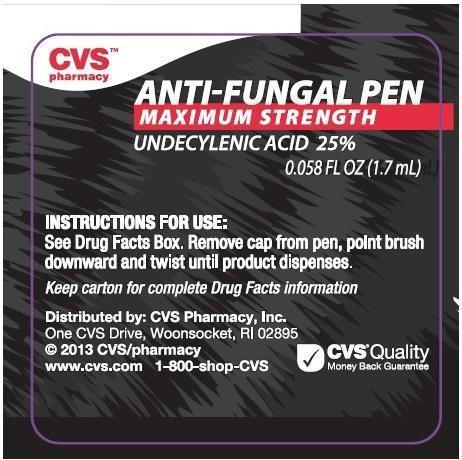 DRUG LABEL: CVS Pharmacy
NDC: 59779-965 | Form: LIQUID
Manufacturer: CVS Pharmacy
Category: otc | Type: HUMAN OTC DRUG LABEL
Date: 20190111

ACTIVE INGREDIENTS: UNDECYLENIC ACID 250 mg/1 mL
INACTIVE INGREDIENTS: ISOPROPYL PALMITATE; PROPYLPARABEN

CVS Pharmacy Anti-Fungal Pen Maximum Strength - Drug Facts

Active Ingredient

Undecylenic Acid 25%

Purpose

Anti-fungal

Uses

For the cure of most:

- ringworm (tinea corporis)
- athlete’s foot (tinea pedis)

For the relief of:

- itching
- scaling
- crackling
- burning
- redness
- soreness
- irritation and discomfort which may accompany these conditions

Warnings

For external use only

Ask a doctor before use on children under 2 years of age

Do not use on diaper rash

When using this product avoid contact with the eyes

Stop use and ask doctor if

- irritation occurs
- there is no improvement within 4 weeks

Keep out of reach of children. If swallowed, get medical help or contact a Poison Control Center right away.

Directions

- read all warnings and directions
- use only as directed
- clean the affected area with soap and water and dry thoroughly
- remove cap from pen
- twist the base of the pen, with brush pointing downward, until product dispenses
- apply a thin layer of the product over the affected area twice daily (morning and night) or as directed by a doctor
- for athlete’s foot, pay special attention to spaces between the toes; wear well-fitting, ventilated shoes, and change shoes and socks at least once daily
- for athlete’s foot and ringworm, use daily for 4 weeks. If condition persists longer, consult a doctor
- intended for use by normally healthy adults only
- persons under 18 years of age or those with highly sensitive or allergic skin should use only as directed by a doctor
- supervise children in the use of this product
- this product is not effective on the scalp or nails

Other Information

- Store at 15°-30C° (59°-86°F)
- Keep cap on pen when not in use

Inactive Ingredients

Isopropyl Palmitate, Propylparaben

Questions or Comments?

1-800-526-FOOT (3668) Mon-Fri 9AM - 5 PM EST

Image of Label and Carton

CVSAntifungalPenLabel.jpg